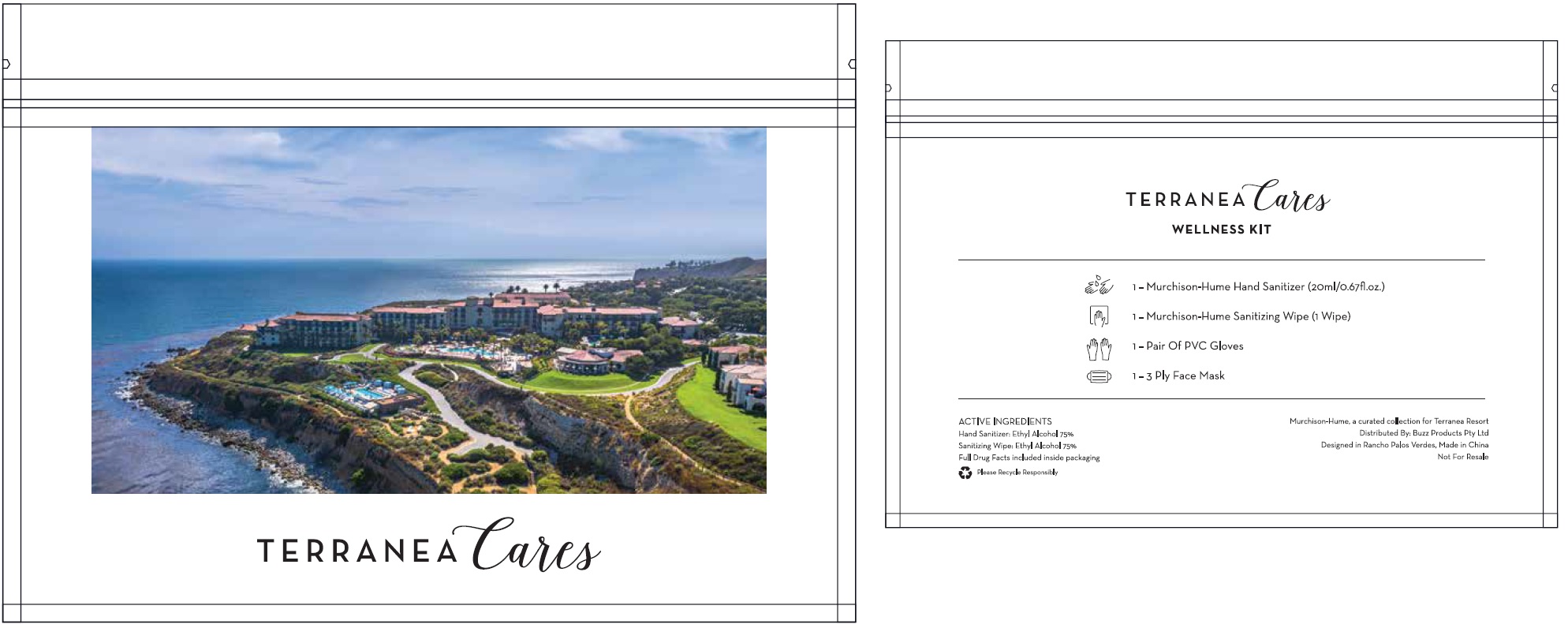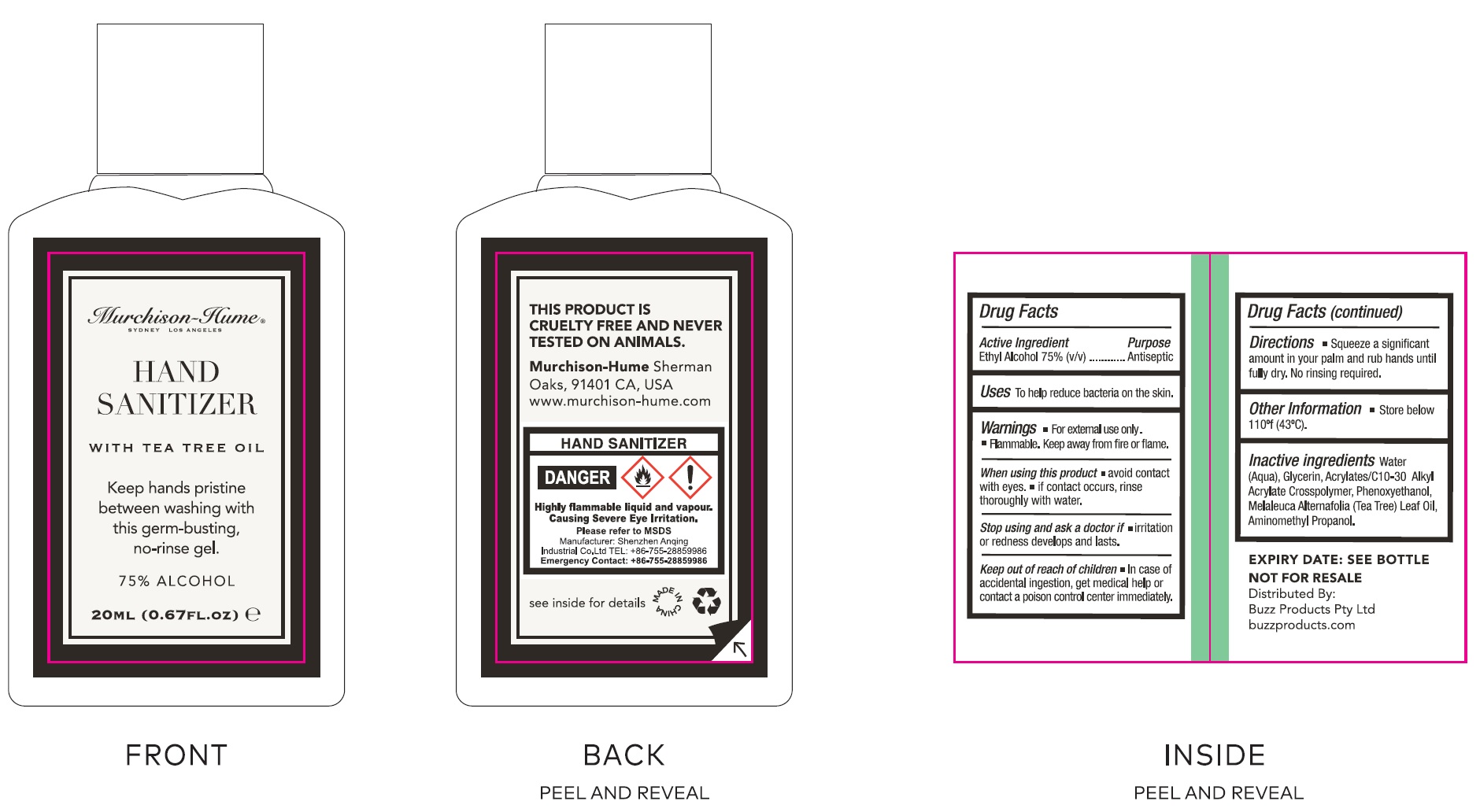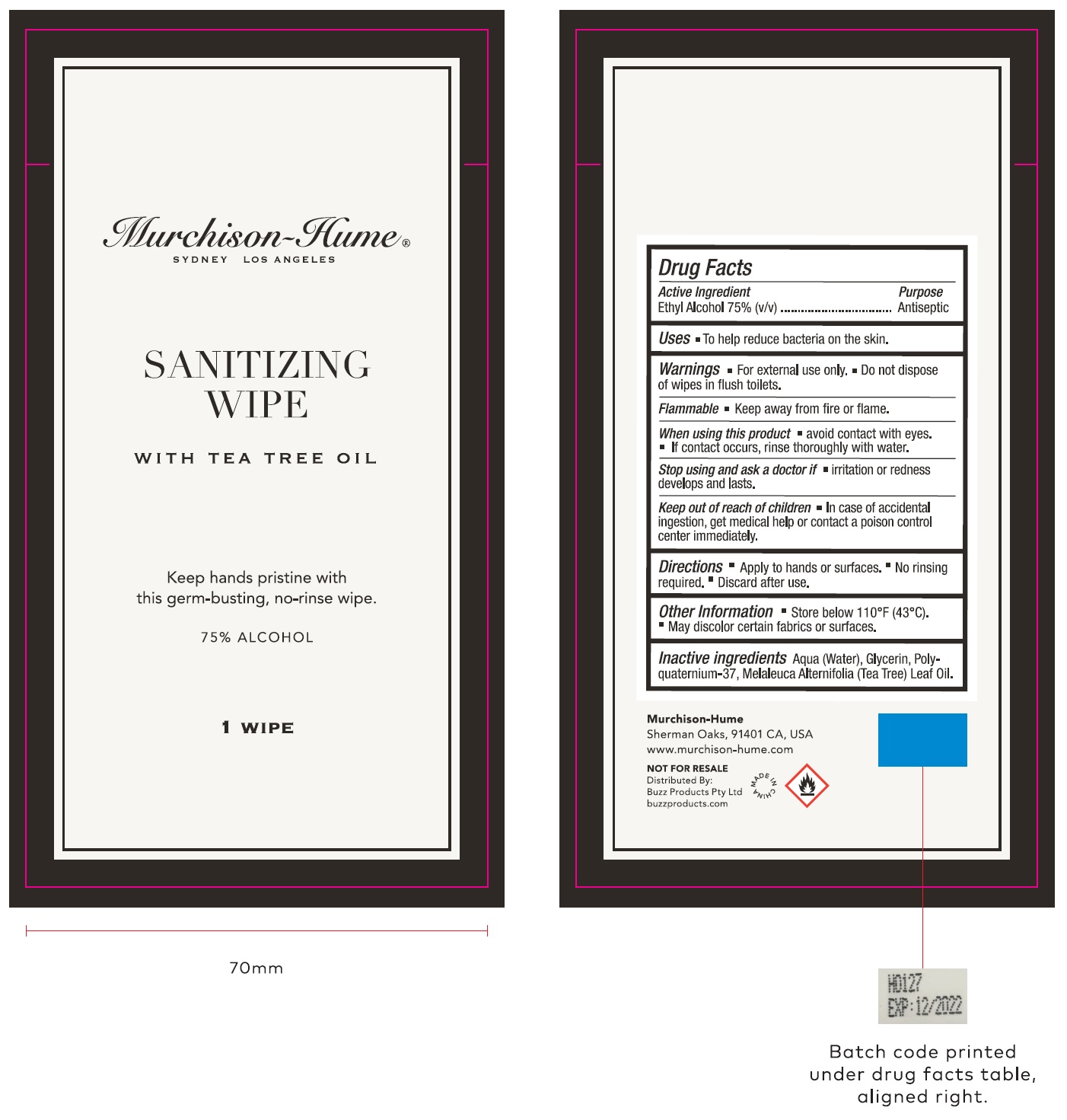 DRUG LABEL: Terranea Cares Wellness Kit
NDC: 69491-304 | Form: KIT | Route: TOPICAL
Manufacturer: Buzz Export Services Pty., Ltd.
Category: otc | Type: HUMAN OTC DRUG LABEL
Date: 20220201

ACTIVE INGREDIENTS: ALCOHOL 0.75 mL/1 mL; ALCOHOL 0.75 mL/1 mL
INACTIVE INGREDIENTS: WATER; GLYCERIN; CARBOMER INTERPOLYMER TYPE A (ALLYL SUCROSE CROSSLINKED); PHENOXYETHANOL; MELALEUCA ALTERNIFOLIA LEAF; AMINOMETHYLPROPANOL; WATER; GLYCERIN; MELALEUCA ALTERNIFOLIA LEAF

Terranea Cares Wellness Kit

Active Ingredient

Ethyl Alcohol 75% (v/v)

Purpose

Antiseptic

Uses

To help reduce bacteria on the skin.

Warnings

- For external use only.
- Flammable. Keep away from fire or flame.

When using this product

- avoid contact with eyes.
- if contact occurs, rinse thoroughly with water.

Stop using and ask a doctor if

irritation or redness develops and lasts.

Keep out of reach of children

In case of accidental ingestion, get medical help or contact a poison control center immediately.

Directions

- Squeeze a significant amount in your palm and rub hands until full dry. No rinsing required.

Other Information

- Store below 110°f (43°C).

Inactive ingredients

Water (Aqua), Glycerin, Acrylates/C-10-30 Alkyl Acrylate Crosspolymer, Phenoxyethanol, Melaleuca Alternafolia (Tea Tree) Leaf Oil, Aminomethyl Propanol.

Active Ingredient

Ethyl Alcohol 75% (v/v)

Purpose

Antiseptic

Uses

- To help reduce bacteria on the skin.

Warnings

- For external use only.
- Do not dispose of wipes in flush toilets.

Flammable

- Keep away from fire or flame.

When using this product

- avoid contact with eyes.
- if contact occurs, rinse thoroughly with water.

Stop using and ask a doctor if

- irritation or redness develops and lasts.

Keep out of reach of children

- In case of accidental ingestion, get medical help or contact a poison control center immediately.

Directions

Apply to hands or surfaces.
No rinsing required.
Discard after use.

Other Information

- Store below 110°F (43°C).
- May discolor certain fabrics or surfaces.

Inactive ingredients

Aqua (Water), Glycerin. Polyquaternium-37, Melaleuca Alternifolia (Tea Tree) Leaf Oil.